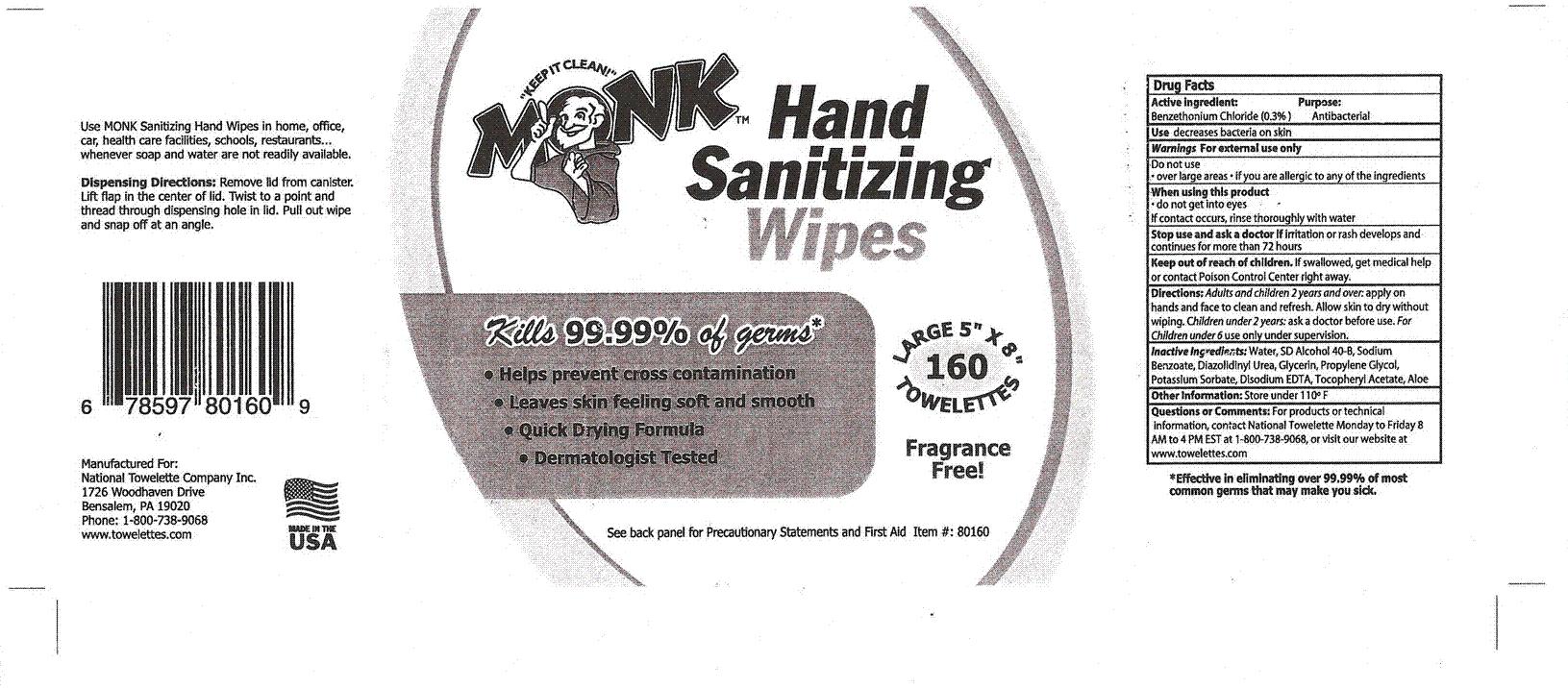 DRUG LABEL: Monk
NDC: 50320-111 | Form: CLOTH
Manufacturer: National Towelette Company 
Category: otc | Type: HUMAN OTC DRUG LABEL
Date: 20100106

ACTIVE INGREDIENTS: Benzethonium Chloride 30 mL/1000 mL
INACTIVE INGREDIENTS: Water 879 mL/1000 mL; Ethanol 111.60 mL/1000 mL; Sodium Benzoate 1.30 mL/1000 mL; Diazolidinylurea 1.30 mL/1000 mL; Glycerin 1.00 mL/1000 mL; Propylene Glycol 1.00 mL/1000 mL; Potassium Sorbate .75 mL/1000 mL; Edetate Disodium .45 mL/1000 mL; Alpha-Tocopherol Acetate 0.10 mL/1000 mL; Aloe 0.09 mL/1000 mL

Image of Label

Principal Display Panel

MM1

Active Ingredients:
Benzethonium Chloride (0.3%)

Purpose:

Antibacterial

DOSAGE AND ADMINISTRATION

Use decreases bacteria on skin

Warnings For external use only

Do not use

- over large areas
- If you are allergic to any of the ingredients

When using this product

- do not get into eyes

If contact occurs, rinse thoroughly with water

Stop use and ask a doctor if irritation or rash develops and continues for more than 72 hours

Keep out of reach of children. If swallowed, get medical help or contact Poison Control Center right away.

DOSAGE AND ADMINISTRATION

Directions: Adults and children 2 years and over: apply on hands and face to clean and refresh. Allow skin to dry without wiping. Children under 2 years: as a doctor before use. For Children under 6 use only under supervision.

INACTIVE INGREDIENT

Inactive Ingredients: Water, SD Alcohol 40-B, Sodium Benzoate, Diazolidinyl Urea, Glycerin, Propylene Glycol, Potassium Sorbate, Disodium EDTA, Tocopheryl Acetate, Aloe

STORAGE AND HANDLING

Store under 110 F

QUESTIONS

Questions and Comments: For products or technical information, contact National Towelette Monday to Friday 8 AM to 4 PM EST at 1-800-738-9068, or visit our website at www.towelettes.com